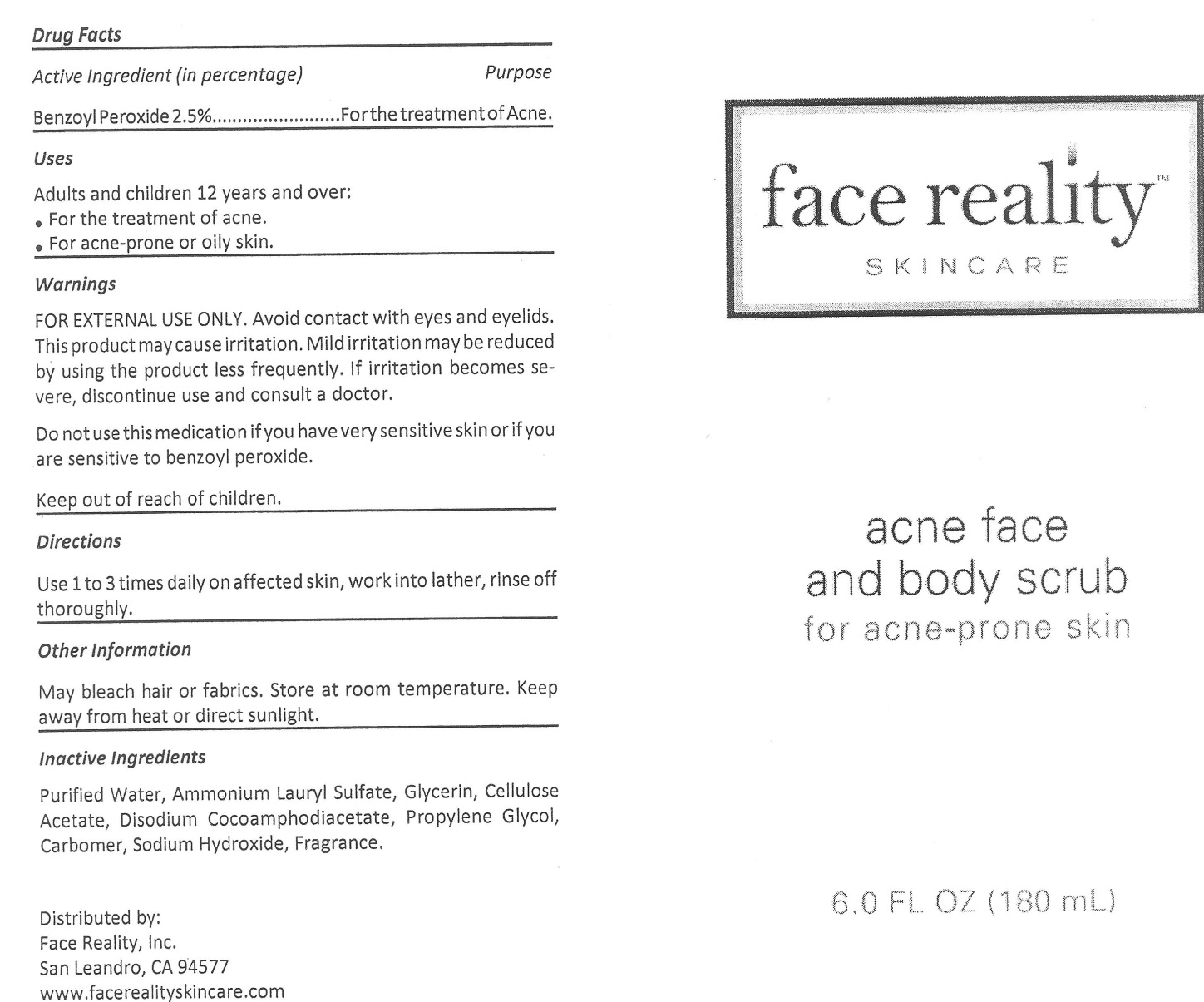 DRUG LABEL: Acne Face and Body
NDC: 70707-101 | Form: SHAMPOO, SUSPENSION
Manufacturer: Face Reality, Inc.
Category: otc | Type: HUMAN OTC DRUG LABEL
Date: 20231215

ACTIVE INGREDIENTS: BENZOYL PEROXIDE 25 mg/1 mL
INACTIVE INGREDIENTS: WATER; AMMONIUM LAURYL SULFATE; GLYCERIN; CELLULOSE ACETATE; DISODIUM COCOAMPHODIACETATE; PROPYLENE GLYCOL; CARBOXYPOLYMETHYLENE; SODIUM HYDROXIDE

Acne Face and Body Scrub

Active Ingredient

Benzoyl Peroxide 2.5%

Purpose

For the treatment of Acne

Uses

Adults and children 12 years and over:

- For the treatment of acne.
- For acne-prone or oily skin.

Warnings

FOR EXTERNAL USE ONLY. Avoid contact with eyes and eyelids. This product may cause irritation. Mild irritation may be reduced by using the product less frequently. If irritation becomes severe, discontinue use and consult a doctor.

Do not use

this medication if you have very sensitive skin or if you are sensitive to benzoly peroxide.

Directions

Use 1 to 3 times daily on affected skin, work into lather, rinse off thoroughly.

Other Information

May bleach hair or fabrics. Store at room temperature. Keep away from heat or direct sunlight.

Inactive Ingredients

Purified Water, Ammonium Lauryl Sulfate, Glycerin, Cellulose Acetate, Disodium Cocoamphodiacetate, Propylene Glycol, Carbomer, Sodium Hydroxide, Fragrance.